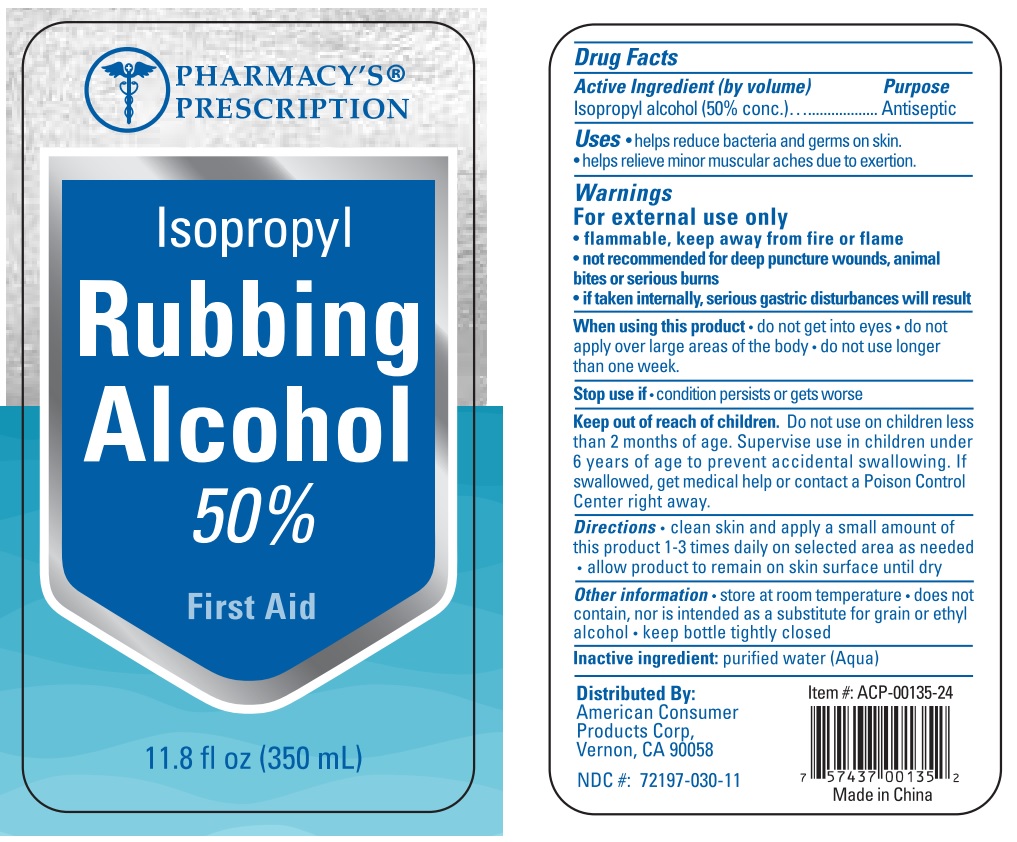 DRUG LABEL: Pharmacys Prescription Rubbing Alcohol
NDC: 72197-030 | Form: LIQUID
Manufacturer: American Consumer Products Corp
Category: otc | Type: HUMAN OTC DRUG LABEL
Date: 20200702

ACTIVE INGREDIENTS: ISOPROPYL ALCOHOL 50 mL/100 mL
INACTIVE INGREDIENTS: WATER

Pharmacys Prescription Rubbing Alcohol

Active Ingredient

Active Ingredient (by volume)

Isopropyl alcohol (50% conc.)

Purpose

Antiseptic

Uses

● helps reduce bacteria and germs on skin.
● helps relieve minor muscular aches due to exertion.

Warnings

For external use only

● flammable, keep away from fire or flame

● not recommended for deep puncture wounds, animal bites or serious burns

● if taken internally, serious gastric disturbances will result

When using this product ● do not get into eyes ● do not apply over large areas of
the body ● do not use longer than one week.

Stop use

Stop use if ● condition persists or gets worse

Keep out of reach of children. Do not use on children less than 2 months of age.
Supervise use in children under 6 years of age to prevent accidental swallowing.
If swallowed, get medical help or contact a Poison Control Center right away.

Directions

Directions ●clean skin and apply a small amount of this product 1-3 times daily on a selected area as needed ● allow product to remain on skin surface until dry

Inactive ingredient

Inactive ingredient: purified water (Aqua)